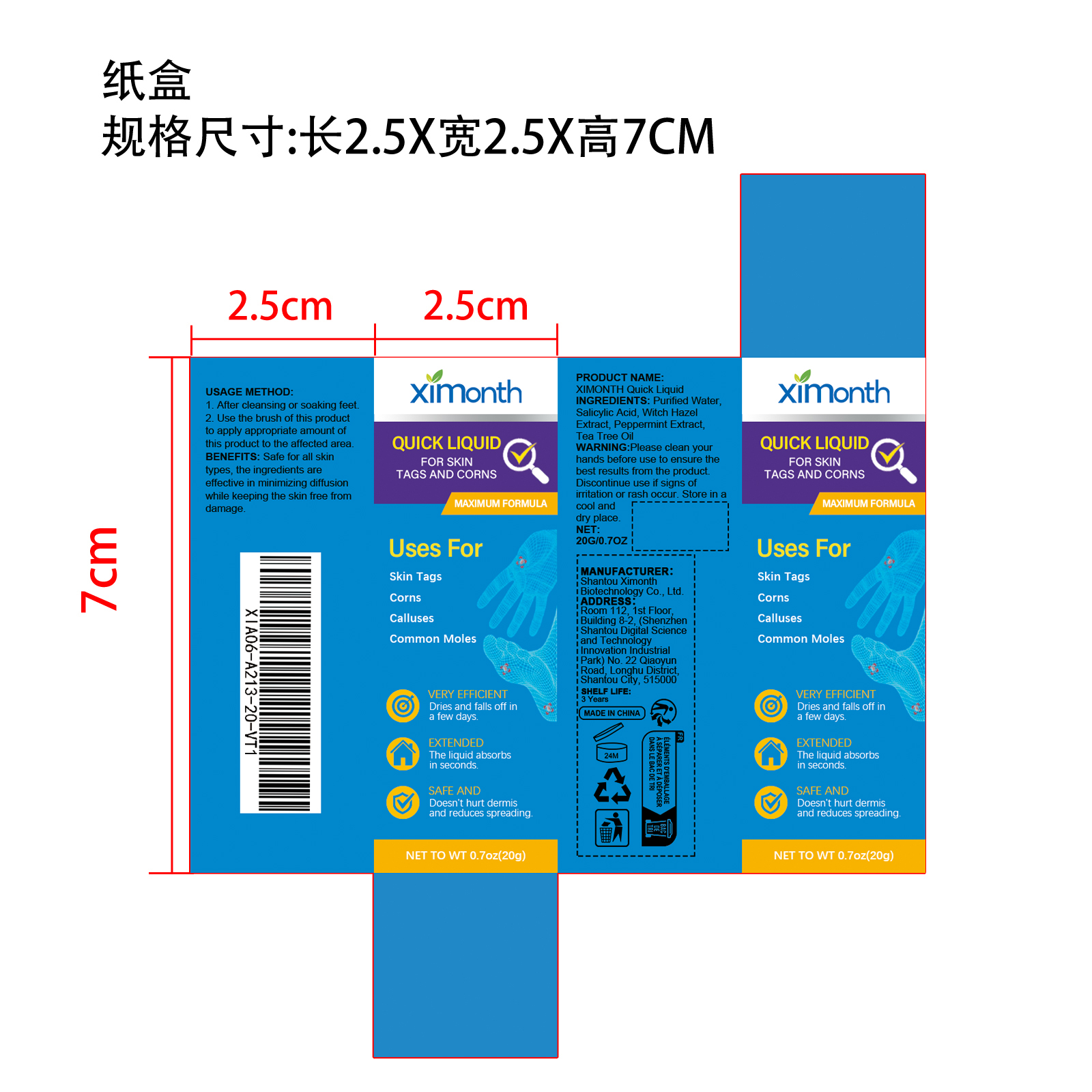 DRUG LABEL: XIMONTH Quick Essence
NDC: 84989-012 | Form: LIQUID
Manufacturer: Shantou Ximonth Biotechnology Co., Ltd.
Category: otc | Type: HUMAN OTC DRUG LABEL
Date: 20251126

ACTIVE INGREDIENTS: TEA TREE OIL 0.04 mg/20 mg; PEPPERMINT 0.1 mg/20 mg; WITCH HAZEL 0.6 mg/20 mg
INACTIVE INGREDIENTS: WATER 19.1 mg/20 mg; SALICYLIC ACID 0.16 mg/20 mg

Active Ingredient(s)

Witch Hazel Extract、Peppermint Extract、Tea Tree Oil

Purpose

Safe for all skin types, the ingredients are effective in minimizing diffusion while keeping the skin free from damage.

Use

1. After cleansing or soaking feet

2. Use the brush of this product to apply appropriate amount of this product to the affected area

Warnings

Please clean your hands before use to ensure the best results from the product. Discontinue use if signs of irritation or rash occur.Store in a cool and dry place.

Do not use

Discontinue use if signs of imitation or rash occur

Stop Use

Discontinue use if signs of imitation or rash occur

KEEP OUT OF REACH OF CHILDREN

Please keep out of reach of children. Do not swallow

STORAGE AND HANDLING

Store in a cool and dry place.

INACTIVE INGREDIENT

Purified Water、Salicylic Acid

INDICATIONS AND USAGE

1. After cleansing or soaking feet.

2. Use the brush of this product to apply appropriate amount of this product to the affected area.

DOSAGE AND ADMINISTRATION

1. After cleansing or soaking feet.

2. Use the brush of this product to apply appropriate amount of this product to the affected area.